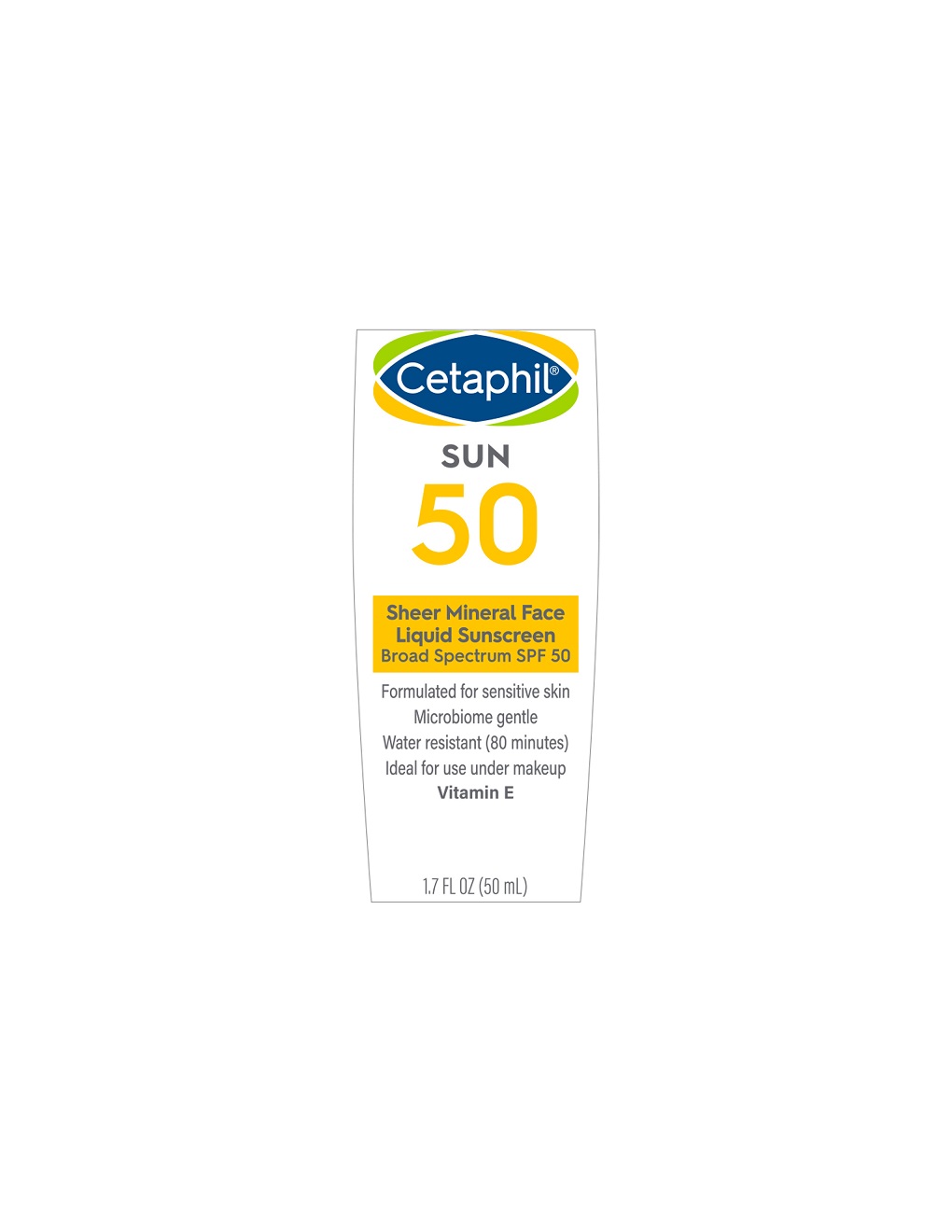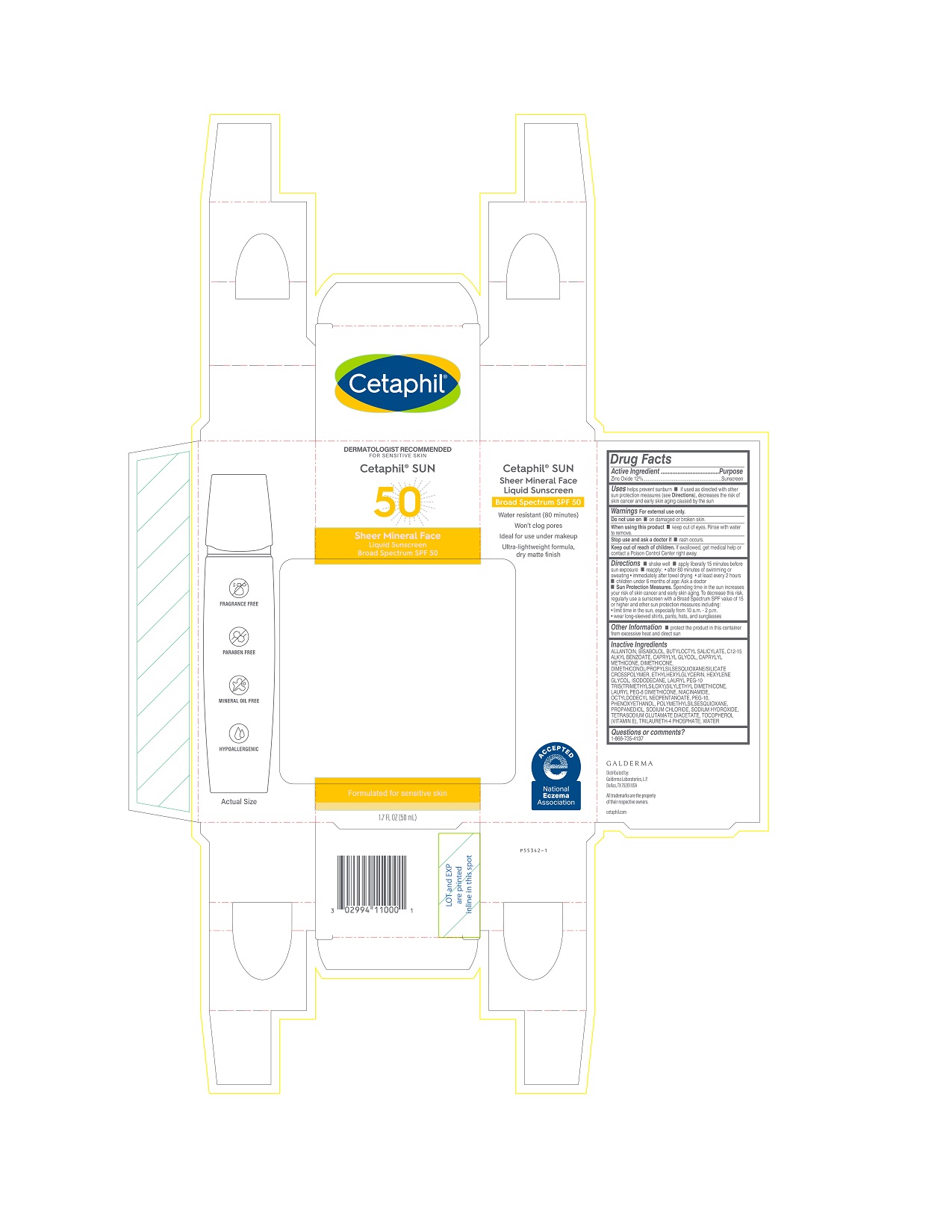 DRUG LABEL: Cetaphil Sheer Mineral Face Liquid Sunscreen SPF 50
NDC: 0299-4110 | Form: LOTION
Manufacturer: Galderma Laboratories, L.P.
Category: otc | Type: HUMAN OTC DRUG LABEL
Date: 20231114

ACTIVE INGREDIENTS: Zinc Oxide 120 mg/1 mL
INACTIVE INGREDIENTS: Allantoin; Levomenol; Butyloctyl Salicylate; Alkyl (C12-15) Benzoate; Caprylyl Glycol; Caprylyl Trisiloxane; Dimethicone; Dimethiconol/Propylsilsesquioxane/Silicate Crosspolymer (450000000 Mw); Ethylhexylglycerin; Hexylene Glycol; Isododecane; Niacinamide; Octyldodecyl Neopentanoate; Polyethylene Glycol 500; Phenoxyethanol; Polymethylsilsesquioxane (4.5 Microns); Propanediol; Sodium Chloride; Sodium Hydroxide; Tetrasodium Glutamate Diacetate; Tocopherol; Trilaureth-4 Phosphate; Water

Cetaphil Sheer Mineral Face Liquid Sunscreen SPF 50

Active Ingredients

Zinc Oxide 12%

PURPOSE

Sunscreen

Uses

- helps prevent sunburn
- if used as directed with other sun protection measures (see Directions), decreases the risk of skin cancer and early skin aging caused by the sun

Do not use

▪ on damaged or broken skin

When using this product

• keep out of eyes. Rinse with water to remove.

Stop use and ask a doctor if

• rash occurs.

Keep out of reach of children.

If swallowed, get medical help or contact a Poison Control Center right away.

Directions

- shake well
- apply liberally 15 minutes before sun exposure
- reapply:
  - after 80 minutes of swimming or sweating
  - immediately after towel drying
  - at least every 2 hours
- children under 6 months of age: Ask a doctor
- Sun Protection Measures. Spending time in the sun increases your risk of skin cancer and early skin aging. To decrease this risk, regularly use a sunscreen with a Broad Spectrum SPF value of 15 or higher and other sun protection measures including:
  - limit time in the sun, especially from 10 a.m. - 2 p.m.
  - wear long-sleeved shirts, pants, hats, and sunglasses

Other Information
▪ protect the product in this container from excessive heat and direct sun

Inactive Ingredients

ALLANTOIN, BISABOLOL, BUTYLOCTYL SALICYLATE, C12-15 ALKYL BENZOATE, CAPRYLYL GLYCOL, CAPRYLYL METHICONE, DIMETHICONE, DIMETHICONOL/PROPYLSILSESQUIOXANE/SILICATE CROSSPOLYMER, ETHYLHEXYLGLYCERIN, HEXYLENE GLYCOL, ISODODECANE, LAURYL PEG-10 TRIS(TRIMETHYLSILOXY)SILYLETHYL DIMETHICONE, LAURYL PEG-8 DIMETHICONE, NIACINAMIDE, OCTYLDODECYL NEOPENTANOATE, PEG-10, PHENOXYETHANOL, POLYMETHYLSILSESQUIOXANE, PROPANEDIOL, SODIUM CHLORIDE,SODIUM HYDROXIDE, TETRASODIUM GLUTAMATE DIACETATE, TOCOPHEROL (VITAMIN E), TRILAURETH-4 PHOSPHATE, WATER

Questions or comments?

1-866-735-4137

PRINCIPAL DISPLAY PANEL - 1.7 FL OZ CARTON

DERMATOLOGIST RECOMMENDED
FOR SENSITIVE SKIN
Cetaphil® SUN
50

Sheer Mineral Face
Liquid Sunscreen

Broad Spectrum SPF 50

Formulated for sensitive skin

1.7 FL OZ (50 mL)

Distributed by:
Galderma Laboratories, L.P.
Dallas, TX 75201 USA
All trademarks are the property of their respective owners.
cetaphil.com
P55342-1

PRINCIPAL DISPLAY PANEL - 1.7 FL OZ FRONT LABEL

Cetaphil®

SUN
50

Sheer Mineral Face
Liquid Sunscreen
Broad Spectrum SPF 50

Formulated for sensitive skin
Microbiome gentle
Water resistant (80 minutes)
Ideal for use under makeup
Vitamin E
1.7 FL OZ (50mL)
P55341-1